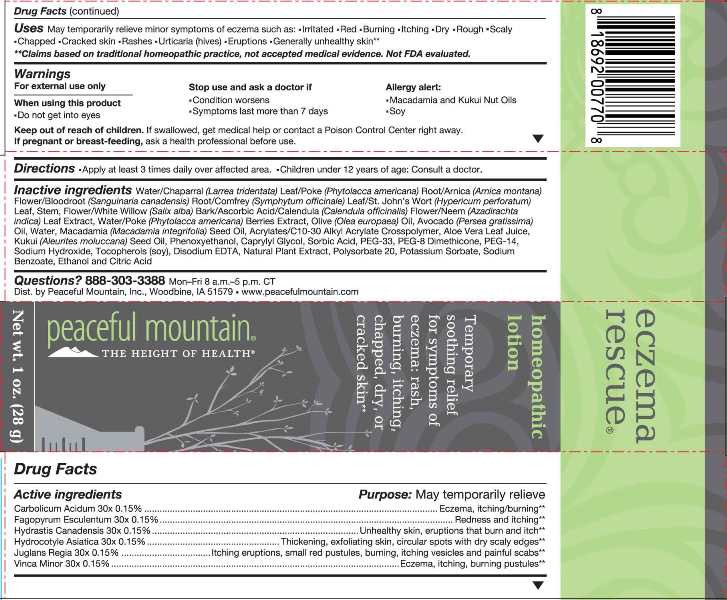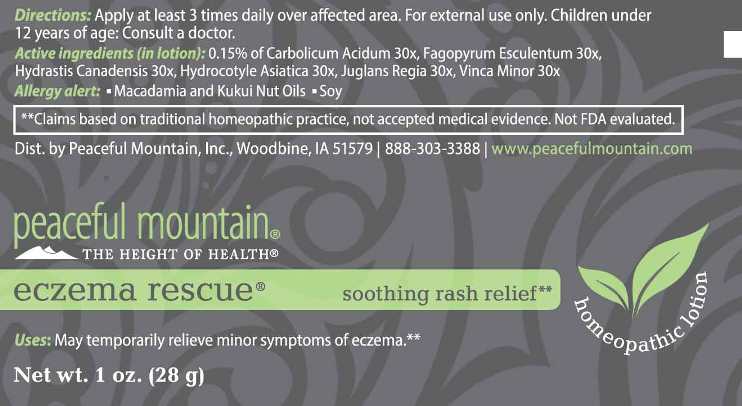 DRUG LABEL: Eczema Rescue
NDC: 43846-0008 | Form: LOTION
Manufacturer: Peaceful Mountain, Inc.
Category: homeopathic | Type: HUMAN OTC DRUG LABEL
Date: 20210617

ACTIVE INGREDIENTS: PHENOL 30 [hp_X]/1 g; FAGOPYRUM ESCULENTUM 30 [hp_X]/1 g; GOLDENSEAL 30 [hp_X]/1 g; CENTELLA ASIATICA 30 [hp_X]/1 g; JUGLANS REGIA LEAF 30 [hp_X]/1 g; JUGLANS REGIA FRUIT RIND, IMMATURE 30 [hp_X]/1 g; VINCA MINOR 30 [hp_X]/1 g
INACTIVE INGREDIENTS: WATER; PHYTOLACCA AMERICANA FRUIT; OLIVE OIL; AVOCADO OIL; MACADAMIA OIL; PHENOXYETHANOL; CAPRYLYL GLYCOL; SORBIC ACID; CARBOMER INTERPOLYMER TYPE A (ALLYL SUCROSE CROSSLINKED); ALOE VERA LEAF; POLYETHYLENE GLYCOL 1500; PEG-8 DIMETHICONE; POLYETHYLENE GLYCOL 700; KUKUI NUT OIL; POLYSORBATE 20; LARREA TRIDENTATA LEAF; PHYTOLACCA AMERICANA ROOT; SODIUM HYDROXIDE; ARNICA MONTANA FLOWER; HYPERICUM PERFORATUM; SALIX ALBA BARK; SANGUINARIA CANADENSIS ROOT; COMFREY LEAF; ASCORBIC ACID; AZADIRACHTA INDICA LEAF; CALENDULA OFFICINALIS FLOWER; .ALPHA.-TOCOPHEROL; EDETATE DISODIUM; OREGANO; POTASSIUM SORBATE; SODIUM BENZOATE; CITRIC ACID MONOHYDRATE; ALCOHOL

Drug Facts:

ACTIVE INGREDIENTS:

(in lotion): 0.15% of Carbolicum Acidum 30X, Fagopyrum Esculentum 30X, Hydrastis Canadensis 30X, Hydrocotyle Asiatica 30X, Juglans Regia 30X, Vinca Minor 30X.

INDICATIONS:

May temporarily relieve minor symptoms of eczema such as • Irritated • Red • Burning •Itching •Dry •Rough •Scaly •Chapped •Cracked skin •Rashes •Urticaria (hives) •Eruptions •Generally unhealthy skin.**

**Claims based on traditional homeopathic practice, not accepted medical evidence. Not FDA evaluated.

WARNINGS:

For external use only

When using this product • Do not get into eyes

Stop use and ask a doctor if • Condition worsens • Symptoms last more than 7 days

Allergy alert: Macadamia and Kukui Nut Oils • Soy

Keep out of reach of children. If swallowed, get medical help or contact a Poison Control Center right away.

If pregnant or breast-feeding, ask a health professional before use.

Keep out of reach of children. If swallowed, get medical help or contact a Poison Control Center right away.

DIRECTIONS:

Apply at least 3 times daily over affected area. For external use only.

Children under 12 years of age: Consult a doctor.

INDICATIONS:

May temporarily relieve minor symptoms of eczema such as • Irritated • Red • Burning •Itching •Dry •Rough •Scaly •Chapped •Cracked skin •Rashes •Urticaria (hives) •Eruptions •Generally unhealthy skin.**

**Claims based on traditional homeopathic practice, not accepted medical evidence. Not FDA evaluated.

INACTIVE INGREDIENTS:

Purified Water, Poke (Berry) Phytolacca Americana, Olive Oil (Olea Europaea), Avocado Oil (Persea Americana), Macadamia Nut Oil (Macadamia Integrifolia), Phenoxyethanol, Caprylyl Glycol, Sorbic Acid, Acrylates/C10-30alkyl Acrylate Crosspolymer, Aloe Barbadensis Leaf Juice, PEG-33, PEG-8 Dimethicone, PEG-14, Kukui Nut Oil (Aleurites Moluccana, Polysorbate 20, Chaparral (Leaf) Larrea Tridentata, Poke (Root) Phytolacca Americana, Sodium Hydroxide (Solution), Arnica (Flower) Arnica Montana, St. John’s Wort (Aerial Parts) Hypericum Perforatum, White Willow (Bark) Salix Alba, Bloodroot (Root) Sanguinaria Canadensis, Comfrey (Leaf) Symphytum Officinale, Ascorbic Acid (Vitamin C Powder), Neem (Leaf) Azadirachta Indica, Calendula (Flower) Calendula Officinalis, Tocopherols (Vitamin E Oil) From Soy, Edetate Disodium (EDTA), Oregano, Potassium Sorbate, Sodium Benzoate, Ethanol, Citric Acid.

QUESTIONS:

Dist. by Peaceful Mountain, Inc., Woodbine, IA 51579

888-303-3388 Mon thru Fri 8 a.m. - 5 p.m. CT

www.peacefulmountain.com

PACKAGE LABEL DISPLAY:

peaceful mountain

THE HEIGHT OF HEALTH

eczema rescue

soothing rash relief

homeopathic

lotion

Net wt. 1 oz. (28 g)